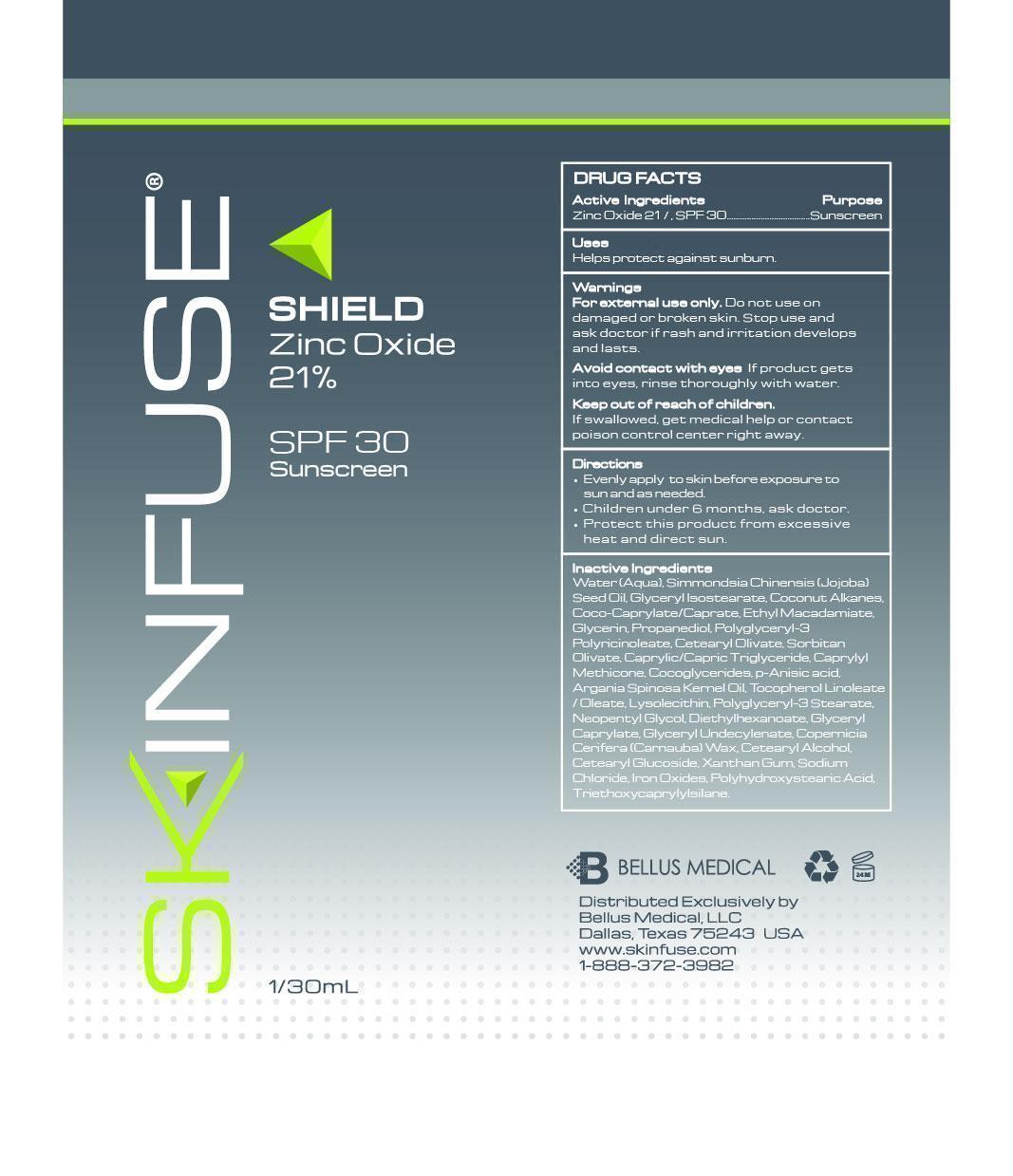 DRUG LABEL: Skinfuse Shield
NDC: 59958-240 | Form: CREAM
Manufacturer: Owen Biosciences, Inc.
Category: otc | Type: HUMAN OTC DRUG LABEL
Date: 20250113

ACTIVE INGREDIENTS: ZINC OXIDE 21 g/100 g
INACTIVE INGREDIENTS: WATER 34 g/100 g; ETHYL MACADAMIATE 5 g/100 g; GLYCERIN 5 g/100 g; PROPANEDIOL 5 g/100 g; POLYGLYCERYL-3 RICINOLEATE 4 g/100 g; JOJOBA OIL 8.97 g/100 g

Skinfuse Shield 30g

Dosage & Administration

Evenly apply to skin before exposure to sun and as needed.

Keep out of reach of children warning

Keep out of reach of children.